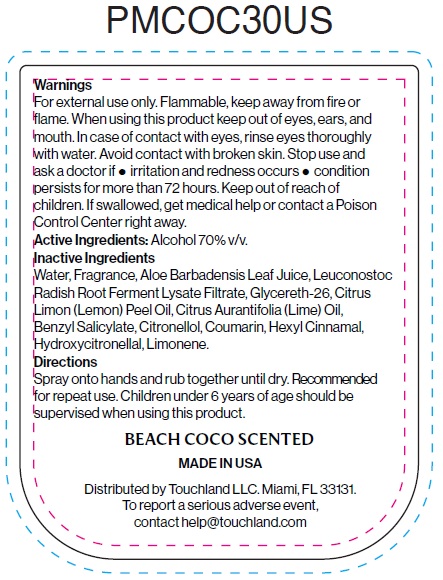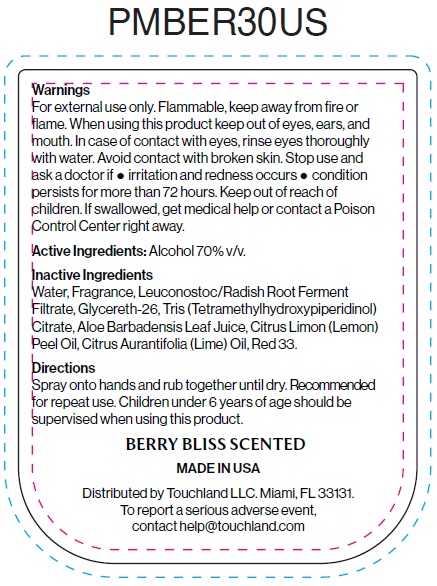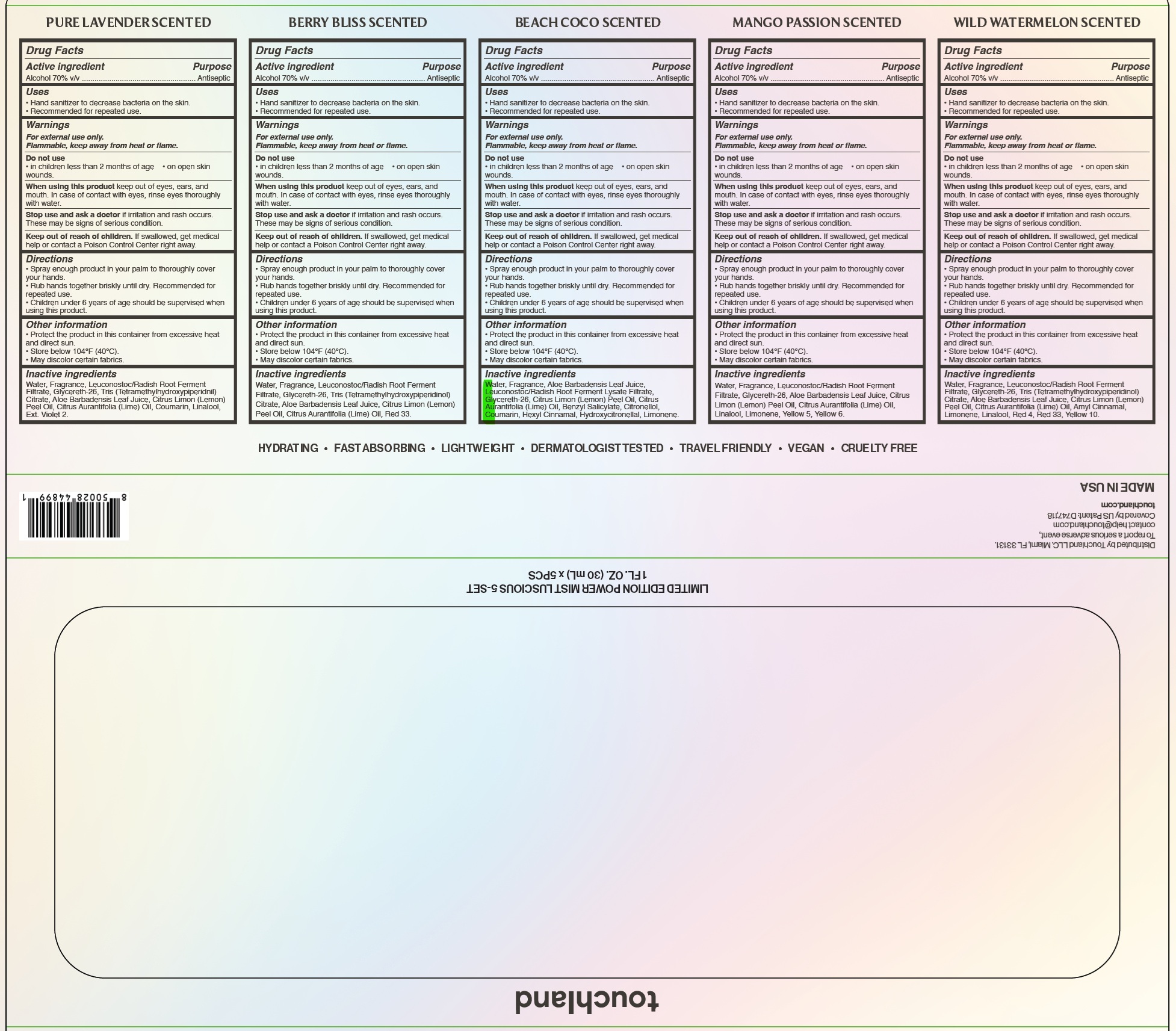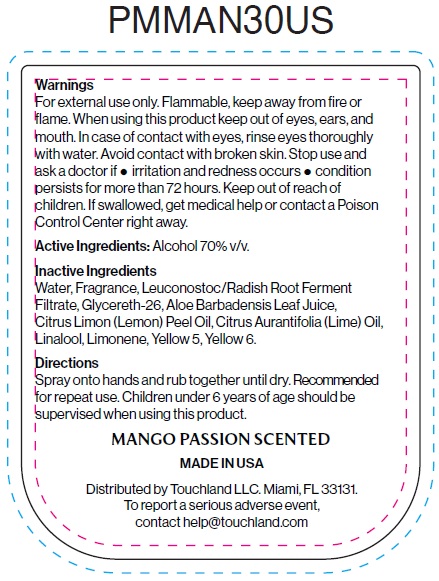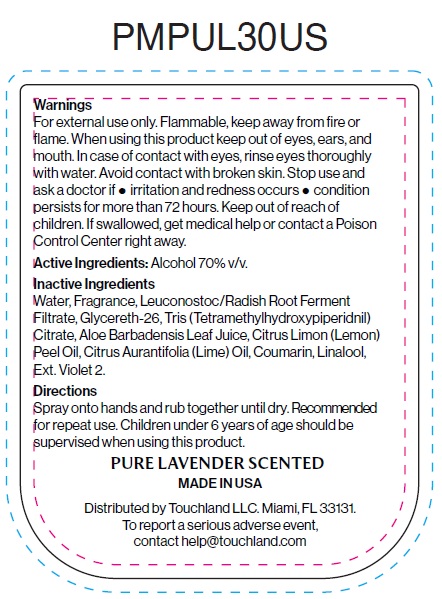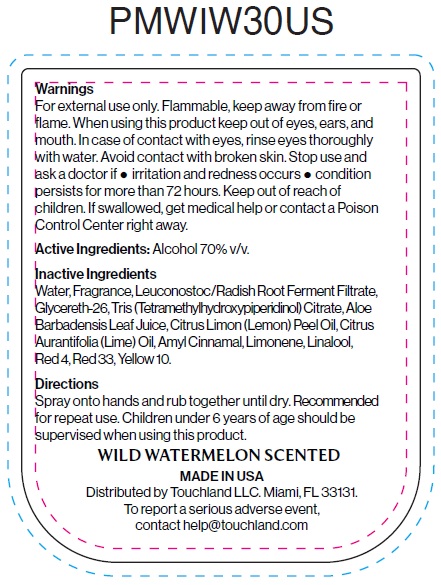 DRUG LABEL: Touchland Power Mist Hydrating Hand Sanitizer Limited Edition Seasonal Five Set
NDC: 72033-149 | Form: KIT | Route: TOPICAL
Manufacturer: TOUCHLAND LLC
Category: otc | Type: HUMAN OTC DRUG LABEL
Date: 20250429

ACTIVE INGREDIENTS: ALCOHOL 70 mL/100 mL; ALCOHOL 70 mL/100 mL; ALCOHOL 70 mL/100 mL; ALCOHOL 70 mL/100 mL; ALCOHOL 70 mL/100 mL
INACTIVE INGREDIENTS: WATER; LEUCONOSTOC/RADISH ROOT FERMENT FILTRATE; GLYCERETH-26; TRIS(TETRAMETHYLHYDROXYPIPERIDINOL) CITRATE; ALOE VERA LEAF JUICE; LEMON OIL, COLD PRESSED; LIME OIL, COLD PRESSED; COUMARIN; LINALOOL, (+/-)-; WATER; LEUCONOSTOC/RADISH ROOT FERMENT FILTRATE; GLYCERETH-26; TRIS(TETRAMETHYLHYDROXYPIPERIDINOL) CITRATE; ALOE VERA LEAF JUICE; LEMON OIL, COLD PRESSED; LIME OIL, COLD PRESSED; D&C RED NO. 33; WATER; ALOE VERA LEAF JUICE; GLYCERETH-26; LEMON OIL, COLD PRESSED; LIME OIL, COLD PRESSED; BENZYL SALICYLATE; .BETA.-CITRONELLOL, (R)-; COUMARIN; .ALPHA.-HEXYLCINNAMALDEHYDE; HYDROXYCITRONELLAL; LIMONENE, (+)-; WATER; LEUCONOSTOC/RADISH ROOT FERMENT FILTRATE; GLYCERETH-26; ALOE VERA LEAF JUICE; LEMON OIL, COLD PRESSED; LIME OIL, COLD PRESSED; LINALOOL, (+/-)-; LIMONENE, (+)-; FD&C YELLOW NO. 5; FD&C YELLOW NO. 6; WATER; LEUCONOSTOC/RADISH ROOT FERMENT FILTRATE; GLYCERETH-26; TRIS(TETRAMETHYLHYDROXYPIPERIDINOL) CITRATE; ALOE VERA LEAF JUICE; LEMON OIL, COLD PRESSED; LIME OIL, COLD PRESSED; .ALPHA.-AMYLCINNAMALDEHYDE; LIMONENE, (+)-; LINALOOL, (+/-)-; FD&C RED NO. 4; D&C RED NO. 33; D&C YELLOW NO. 10

Touchland Power Mist Hydrating Hand Sanitizer Limited Edition Seasonal Five Set

Active ingredient

Alcohol 70% v/v

Purpose

Antiseptic

Uses

- Hand sanitizer to decrease bacteria on the skin.
- Recommended for repeated use.

Warnings

For external use only.
Flammable, keep away from heat or flame.

Do not use

- in children less than 2 months of age
- on open skin wounds.

When using this product

keep out of eyes, ears, and mouth. In case of contact with eyes, rinse eyes thoroughly with water.

Stop use and ask a doctor

if irritation and rash occurs. These may be signs of serious condition.

Keep out of reach of children.

If swallowed, get medical help or contact a Poison Control Center right away.

Directions

- Spray enough product in your palm to thoroughly cover your hands.
- Rub hands together briskly until dry. Recommended for repeated use.
- Children under 6 years of age should be supervised when using this product.

Other information

- Protect the product in this container from excessive heat and direct sun.
- Store below 104°F (40°C).
- May discolor certain fabrics.

Inactive ingredients

Water, Fragrance, Leuconostoc/Radish Root Ferment Filtrate, Glycereth-26, Tris (Tetramethylhydroxypiperidnil) Citrate, Aloe Barbadensis Leaf Juice, Citrus Limon (Lemon) Peel Oil, Citrus Aurantifolia (Lime) Oil, Coumarin, Linalool, Ext. Violet 2.

Active ingredient

Alcohol 70% v/v

Purpose

Antiseptic

Uses

- Hand sanitizer to decrease bacteria on the skin.
- Recommended for repeated use.

Warnings

For external use only.
Flammable, keep away from heat or flame.

Do not use

- in children less than 2 months of age
- on open skin wounds.

When using this product

keep out of eyes, ears, and mouth. In case of contact with eyes, rinse eyes thoroughly with water.

Stop use and ask a doctor

if irritation and rash occurs. These may be signs of serious condition.

Keep out of reach of children.

If swallowed, get medical help or contact a Poison Control Center right away.

Directions

- Spray enough product in your palm to thoroughly cover your hands.
- Rub hands together briskly until dry. Recommended for repeated use.
- Children under 6 years of age should be supervised when using this product.

Other information

- Protect the product in this container from excessive heat and direct sun.
- Store below 104°F (40°C).
- May discolor certain fabrics.

Inactive ingredients

Water, Fragrance, Leuconostoc/Radish Root Ferment Filtrate, Glycereth-26, Tris (Tetramethylhydroxypiperidinol) Citrate, Aloe Barbadensis Leaf Juice, Citrus Limon (Lemon) Peel Oil, Citrus Aurantifolia (Lime) Oil, Red 33.

Active ingredient

Alcohol 70% v/v

Purpose

Antiseptic

Uses

- Hand sanitizer to decrease bacteria on the skin.
- Recommended for repeated use.

Warnings

For external use only.
Flammable, keep away from fire or flame.

Do not use

- in children less than 2 months of age
- on open skin wounds.

When using this product

keep out of eyes, ears, and mouth. In case of contact with eyes, rinse eyes thoroughly with water.

Stop use and ask a doctor

if irritation and rash occurs. These may be signs of serious condition.

Keep out of reach of children.

If swallowed, get medical help or contact a Poison Control Center right away.

Directions

- Spray enough product in your palm to thoroughly cover your hands.
- Rub hands together briskly until dry. Recommended for repeated use.
- Children under 6 years of age should be supervised when using this product.

Other information

- Protect the product in this container from excessive heat and direct sun.
- Store below 104°F (40°C).
- May discolor certain fabrics.

Inactive ingredients

Water, Fragrance, Aloe Barbadensis Leaf Juice, Leuconostoc/Radish Root Ferment Lysate Filtrate, Glycereth-26, Citrus Limon (Lemon) Peel Oil, Citrus Aurantifolia (Lime) Oil, Benzyl Salicylate, Citronellol, Coumarin, Hexyl Cinnamal, Hydroxycitronellal, Limonene.

Active ingredient

Alcohol 70% v/v

Purpose

Antiseptic

Uses

- Hand sanitizer to decrease bacteria on the skin.
- Recommended for repeated use.

Warnings

For external use only.
Flammable, keep away from fire or flame.

Do not use

- in children less than 2 months of age
- on open skin wounds.

When using this product

keep out of eyes, ears, and mouth. In case of contact with eyes, rinse eyes thoroughly with water.

Stop use and ask a doctor

if irritation and rash occurs. These may be signs of serious condition.

Keep out of reach of children.

If swallowed, get medical help or contact a Poison Control Center right away.

Directions

- Spray enough product in your palm to thoroughly cover your hands.
- Rub hands together briskly until dry. Recommended for repeated use.
- Children under 6 years of age should be supervised when using this product.

Other information

- Protect the product in this container from excessive heat and direct sun.
- Store below 104°F (40°C).
- May discolor certain fabrics.

Inactive ingredients

Water, Fragrance, Leuconostoc/Radish Root Ferment Filtrate, Glycereth-26, Aloe Barbadensis Leaf Juice, Citrus Limon (Lemon) Peel Oil, Citrus Aurantifolia (Lime) Oil, Linalool, Limonene, Yellow 5, Yellow 6.

Active ingredient

Alcohol 70% v/v

Purpose

Antiseptic

Uses

- Hand sanitizer to decrease bacteria on the skin.
- Recommended for repeated use.

Warnings

For external use only.
Flammable, keep away from heat or flame.

Do not use

- in children less than 2 months of age
- on open skin wounds.

When using this product

keep out of eyes, ears, and mouth. In case of contact with eyes, rinse eyes thoroughly with water.

Stop use and ask a doctor

if irritation and rash occurs. These may be signs of serious condition.

Keep out of reach of children.

If swallowed, get medical help or contact a Poison Control Center right away.

Directions

- Spray enough product in your palm to thoroughly cover your hands.
- Rub hands together briskly until dry. Recommended for repeated use.
- Children under 6 years of age should be supervised when using this product.

Other information

- Protect the product in this container from excessive heat and direct sun.
- Store below 104°F (40°C).
- May discolor certain fabrics.

Inactive ingredients

Water, Fragrance, Leuconostoc/Radish Root Ferment Filtrate, Glycereth-26, Tris (Tetramethylhydroxypiperidinol) Citrate, Aloe Barbadensis Leaf Juice, Citrus Limon (Lemon) Peel Oil, Citrus Aurantifolia (Lime) Oil, Amyl Cinnamal, Limonene, Linalool, Red 4, Red 33, Yellow 10.